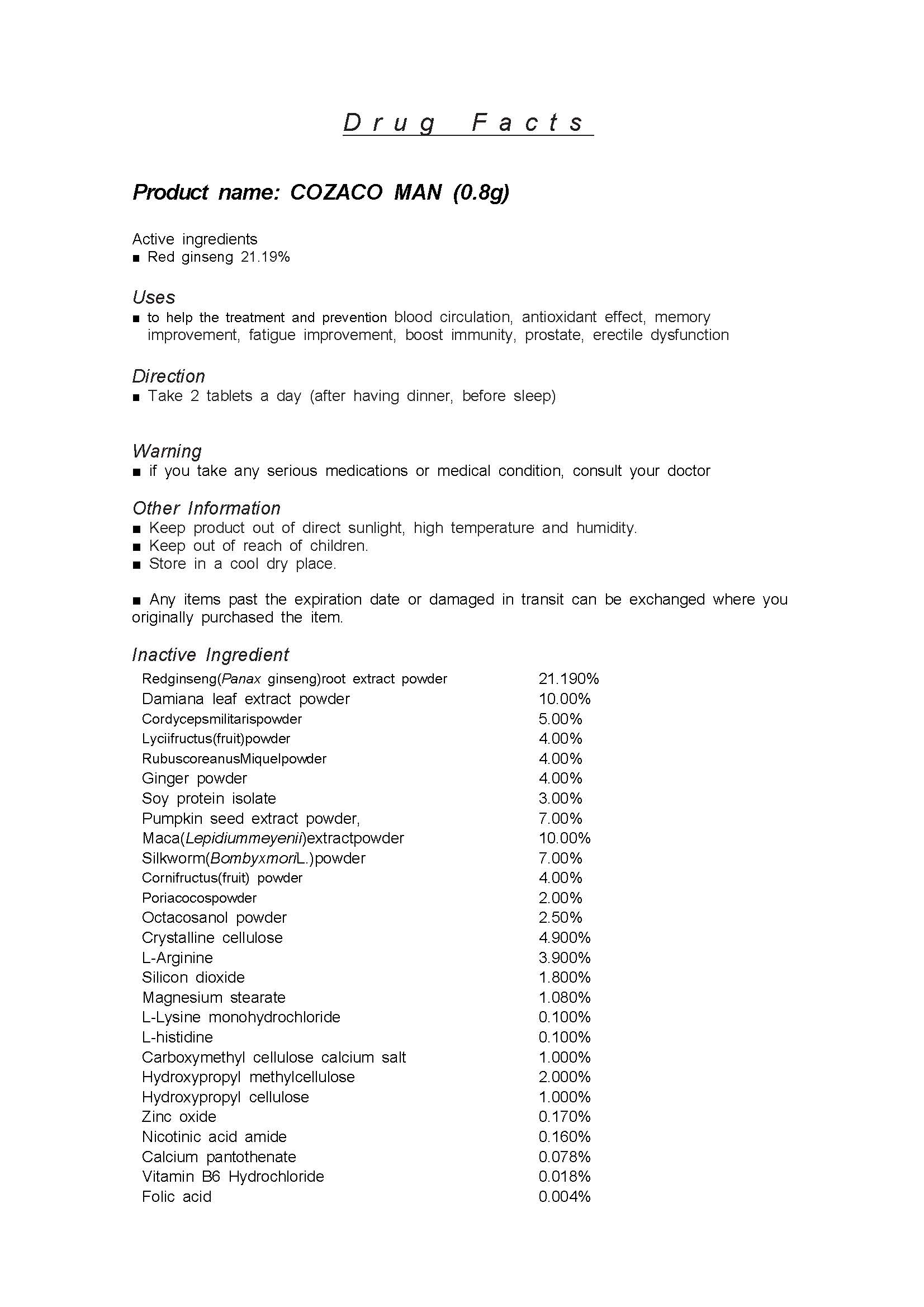 DRUG LABEL: COZACO MAN
NDC: 81651-0001 | Form: TABLET
Manufacturer: Kone Bio Logics Co., Ltd.
Category: otc | Type: HUMAN OTC DRUG LABEL
Date: 20220110

ACTIVE INGREDIENTS: PANAX GINSENG ROOT OIL 21.19 1/1 1
INACTIVE INGREDIENTS: CORDYCEPS MILITARIS WHOLE

ACTIVE INGREDIENT

Red ginseng

INACTIVE INGREDIENT

Damiana leaf extract powder

Cordyceps militaris powder

Lyciifructus(fruit)powder

RubuscoreanusMiquelpowder

Ginger powder

Soy protein isolate

Pumpkin seed extract powder,

Maca(Lepidiummeyenii)extractpowder

Silkworm(BombyxmoriL.)powder

Cornifructus(fruit) powder

Poriacocospowder

Octacosanol powder

Crystalline cellulose

L-Arginine

Silicon dioxide

Magnesium stearate

L-Lysine monohydrochloride

L-histidine

Carboxymethyl cellulose calcium salt

Hydroxypropyl methylcellulose

Hydroxypropyl cellulose

Zinc oxide

Nicotinic acid amide

Calcium pantothenate

Vitamin B6 Hydrochloride

Folic acid

PURPOSE

■ blood circulation, antioxidant effect, memory improvement, fatigue improvement, boost immunity, prostate, erectile dysfunction

KEEP OUT OF REACH OF CHILDREN

WARNING

Please check product ingredients if you have any allergies before taking.

Please be careful during open the product package.

Keep product out of direct sunlight, high temperature and humidity.

Store in a cool dry place.

Any items past the expiration date or damaged in transit can be exchanged where you originally purchased the item.

consult your doctor if any abnormal symptoms occur

USES

for oral use only

INDICATION & USAGE SECTION

Take 2 tablets a day (after having dinner, before sleep)